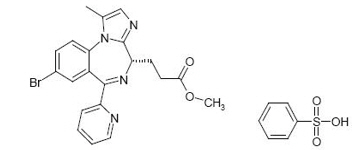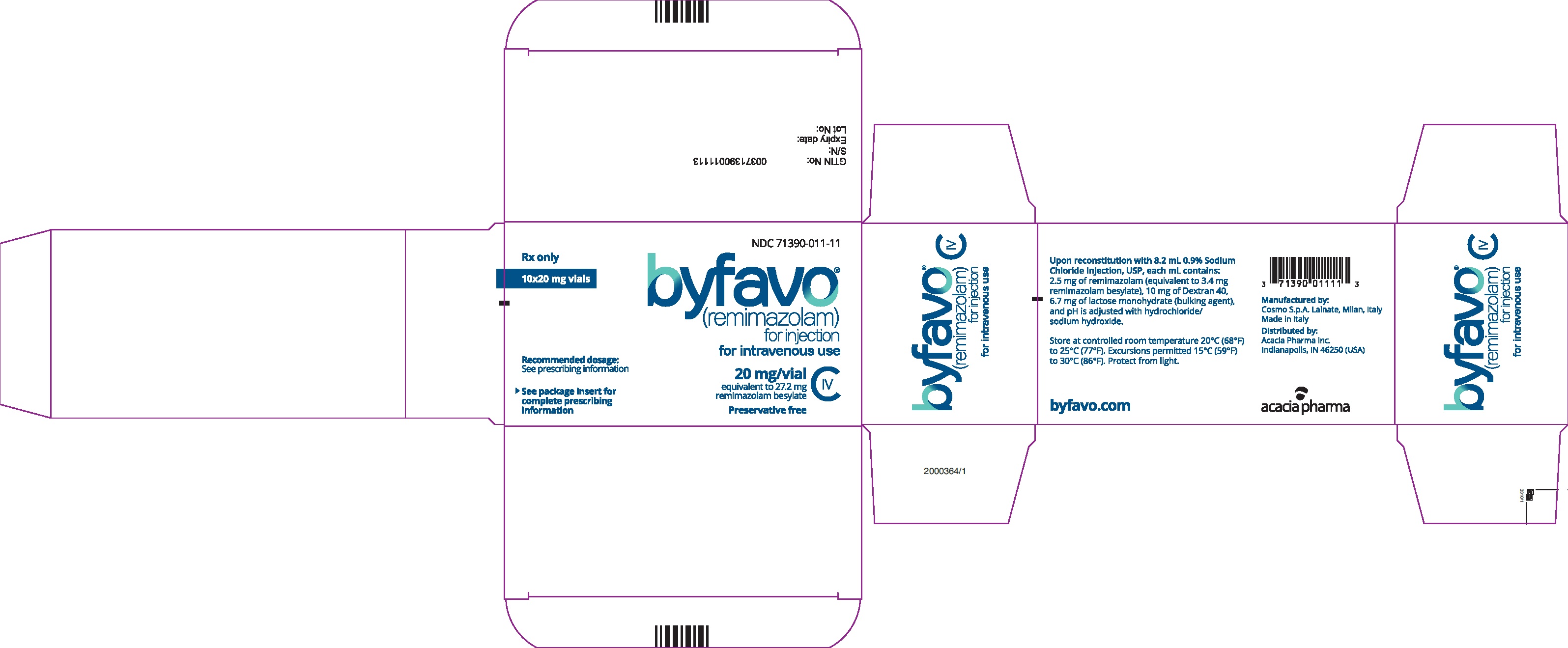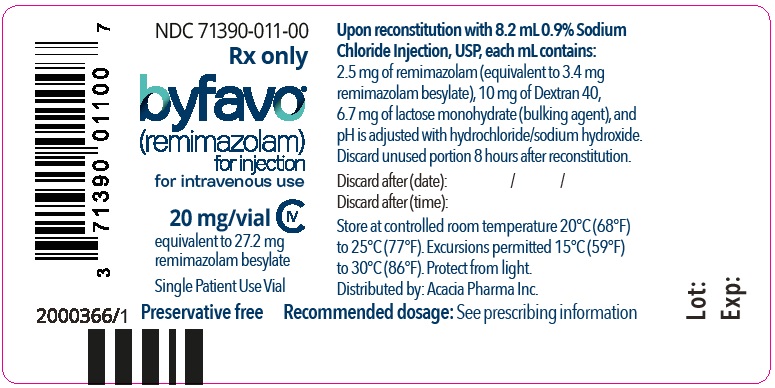 DRUG LABEL: BYFAVO
NDC: 71390-011 | Form: INJECTION, POWDER, LYOPHILIZED, FOR SOLUTION
Manufacturer: Acacia Pharma, Ltd.
Category: prescription | Type: HUMAN PRESCRIPTION DRUG LABEL
Date: 20250220
DEA Schedule: CIV

ACTIVE INGREDIENTS: remimazolam besylate 2.5 mg/1 mL
INACTIVE INGREDIENTS: dextran 40 10 mg/1 mL; lactose monohydrate 6.7 mg/1 mL; HYDROCHLORIC ACID; sodium hydroxide

HIGHLIGHTS OF PRESCRIBING INFORMATION

These highlights do not include all the information needed to use BYFAVO safely and effectively. See full prescribing information for BYFAVO.
BYFAVO® (remimazolam) for injection, for intravenous use, CIV
Initial U.S. Approval: 2020

WARNING: PERSONNEL AND EQUIPMENT FOR MONITORING AND RESUSCITATION, AND RISKS FROM CONCOMITANT USE WITH OPIOID ANALGESICS AND OTHER SEDATIVE-HYPNOTICS

See full prescribing information for complete boxed warning

- Only personnel trained in the administration of procedural sedation, and not involved in the conduct of the diagnostic or therapeutic procedure, should administer BYFAVO. (2.1, 5.1)
- Administering personnel must be trained in the detection and management of airway obstruction, hypoventilation, and apnea, including the maintenance of a patent airway, supportive ventilation, and cardiovascular resuscitation. (2.1, 5.1)
- BYFAVO has been associated with hypoxia, bradycardia, and hypotension. Continuously monitor vital signs during sedation and through the recovery period. (2.1, 5.1)
- Resuscitative drugs, and age- and size-appropriate equipment for bag/valve/mask assisted ventilation must be immediately available during administration of BYFAVO. (2.1, 5.1)
- Concomitant use of benzodiazepines with opioid analgesics may result in profound sedation, respiratory depression, coma, and death. The sedative effect of intravenous BYFAVO can be accentuated by concomitantly administered CNS depressant medications, including other benzodiazepines and propofol. Continuously monitor patients for respiratory depression and depth of sedation. (5.2, 7.1)

RECENT MAJOR CHANGES

Warnings and Precautions (5.4) | 01/2023

1 INDICATIONS AND USAGE

BYFAVO (remimazolam) for injection is a benzodiazepine indicated for the induction and maintenance of procedural sedation in adults undergoing procedures lasting 30 minutes or less. (1)

2 DOSAGE AND ADMINISTRATION

Individualize and titrate BYFAVO dosing to desired clinical effect. (2.2)

Adult Patients:

- Administer an initial dose intravenously as a 5 mg push injection over a 1-minute time period. (2.2)
- If necessary, administer supplemental doses of 2.5 mg intravenously over a 15-second time period. At least 2 minutes must elapse prior to the administration of any supplemental dose. (2.2)

ASA III-IV Patients (at the discretion of the physician):

- Based on the general condition of the patient, administer 2.5 mg to 5 mg over 1-minute time period. (2.2)
- If necessary, administer supplemental doses of 1.25 mg to 2.5 mg intravenously over a 15-second time period. At least 2 minutes must elapse prior to the administration of any supplemental dose. (2.2)

3 DOSAGE FORM AND STRENGTHS

Each glass, single-patient-use vial contains 20 mg BYFAVO (remimazolam) lyophilized powder for reconstitution, equivalent to 27.2 mg remimazolam besylate. (3)

4 CONTRAINDICATIONS

Hypersensitivity to dextran 40. (4)

5 WARNINGS AND PRECAUTIONS

Hypersensitivity Reactions: Hypersensitivity reactions including anaphylaxis may occur. (5.3)

Neonatal Sedation and Withdrawal Syndrome: Receiving benzodiazepines during pregnancy can result in neonatal sedation and/or neonatal withdrawal. (5.4, 8.1)

Pediatric Neurotoxicity: In developing animals, exposures greater than 3 hours cause neurotoxicity. Weigh benefits against potential risks when considering elective procedures in children under 3 years old. (5.5)

6 ADVERSE REACTIONS

The most common adverse reactions (>10%) in patients receiving BYFAVO for procedural sedation are hypotension, hypertension, diastolic hypertension, systolic hypertension, hypoxia, and diastolic hypotension. (6)

To report SUSPECTED ADVERSE REACTIONS, contact Acacia Pharma at 1-877-357-9237 or FDA at 1-800-FDA-1088 or www.fda.gov/medwatch

8 USE IN SPECIFIC POPULATIONS

Lactation: A lactating woman may pump and discard breast milk for 5 hours after treatment with BYFAVO. (8.2)

Pediatric Use: BYFAVO should not be used in patients less than 18 years of age. (8.4)

Geriatric Use: Sedating drugs, such as BYFAVO, may cause confusion and over-sedation in the elderly; elderly patients generally should be observed closely. (8.5)

Severe Hepatic Impairment: In patients with severe hepatic impairment the dose of BYFAVO should be carefully titrated to effect. Depending on the overall status of the patient, reduced doses might be indicated. (8.6, 12.3)

FULL PRESCRIBING INFORMATION

WARNING: PERSONNEL AND EQUIPMENT FOR MONITORING AND RESUSCITATION AND RISKS FROM CONCOMITANT USE WITH OPIOID ANALGESICS

Personnel and Equipment for Monitoring and Resuscitation

- Only personnel trained in the administration of procedural sedation, and not involved in the conduct of the diagnostic or therapeutic procedure, should administer BYFAVO [see Dosage and Administration (2.1), Warnings and Precautions (5.1)].
- Administering personnel must be trained in the detection and management of airway obstruction, hypoventilation, and apnea, including the maintenance of a patent airway, supportive ventilation, and cardiovascular resuscitation [see Dosage and Administration (2.1), Warnings and Precautions (5.1)].
- BYFAVO has been associated with hypoxia, bradycardia, and hypotension. Continuously monitor vital signs during sedation and during the recovery period [see Dosage and Administration (2.1), Warnings and Precautions (5.1)].
- Resuscitative drugs, and age- and size-appropriate equipment for bag/valve/mask assisted ventilation must be immediately available during administration of BYFAVO [see Dosage and Administration (2.1), Warnings and Precautions (5.1)].

Risks From Concomitant Use With Opioid Analgesics and Other Sedative-Hypnotics

Concomitant use of benzodiazepines, including BYFAVO, and opioid analgesics may result in profound sedation, respiratory depression, coma, and death. The sedative effect of intravenous BYFAVO can be accentuated by concomitantly administered CNS depressant medications, including other benzodiazepines and propofol. Continuously monitor patients for respiratory depression and depth of sedation [see Warnings and Precautions (5.2), Drug Interactions (7.1)].

1 INDICATIONS AND USAGE

BYFAVO® is indicated for the induction and maintenance of procedural sedation in adults undergoing procedures lasting 30 minutes or less.

2 DOSAGE AND ADMINISTRATION

2.1 Important Dosage and Administration Instructions

BYFAVO can depress respiration. Continuously monitor patients for early signs of hypoventilation, airway obstruction, and apnea using capnography, pulse oximetry, and clinical assessment.

Only personnel trained in the administration of procedural sedation, and not involved in the conduct of the diagnostic or therapeutic procedure, should administer BYFAVO.

Administering personnel must be trained in the detection and management of airway obstruction, hypoventilation, and apnea, including the maintenance of a patent airway, supportive ventilation, and cardiovascular resuscitation.

Supplemental oxygen, resuscitative drugs, and age- and size-appropriate equipment for bag/valve/mask assisted ventilation must be immediately available during administration of BYFAVO. A benzodiazepine reversal agent should be immediately available.

Continuously monitor vital signs during sedation and through the recovery period [see Warnings and Precautions (5.1)].

Peak sedation occurs approximately 3 to 3.5 minutes after an initial 5 mg intravenous injection of BYFAVO given over a 1-minute period [see Clinical Pharmacology (12.2)].

Titrate subsequent doses of BYFAVO on the basis of clinical judgment and assessment of the depth of sedation. If maintenance of procedural sedation is inadequate, consider alternative medications [see Clinical Studies (14)].

2.2 Basic Dosing Information

- Individualize BYFAVO dosing and titrate to desired clinical response.
- In clinical studies, fentanyl 25 to 75 mcg was administered for analgesia prior to the first dose of BYFAVO. Supplemental doses of fentanyl were administered as needed for analgesia [see Clinical Studies (14)].
- Recommended dosing guidelines:

Induction of Procedural Sedation | For adult patients: Administer 5 mg intravenously over a 1-minute time period.
Induction of Procedural Sedation | For ASA [ASA = American Society of Anesthesiologists Physical Status Classification System] III and IV patients: Administer 2.5 mg to 5 mg intravenously over 1 minute based on the general condition of the patient.
Maintenance of Procedural Sedation (as needed) | For adult patients: Administer 2.5 mg intravenously over 15 seconds. At least 2 minutes must elapse prior to administration of any supplemental dose.
Maintenance of Procedural Sedation (as needed) | For ASA III and IV patients: Administer 1.25 mg to 2.5 mg intravenously over 15 seconds. At least 2 minutes must elapse prior to administration of any supplemental dose.

2.3 Preparation

Reconstitution of BYFAVO (remimazolam) for injection

- Strict aseptic technique must be maintained during handling of BYFAVO.
- This product does not contain preservative.
- Once removed from packaging, protect vials from light.
- Each single-patient-use vial contains 20 mg BYFAVO lyophilized powder for reconstitution. The product must be prepared immediately before use.
- To reconstitute, add 8.2 mL sterile 0.9% Sodium Chloride Injection, USP, to the vial, directing the stream of solution toward the wall of the vial. Gently swirl the vial (do not shake) until the contents are fully dissolved. The reconstituted product will deliver a final concentration of 2.5 mg/mL solution of BYFAVO.
- Parenteral drug products should be inspected visually for particulate matter and discoloration prior to administration. Upon reconstitution, the solution should be a clear, colorless to pale yellow solution. Discard if particulate matter or discoloration is observed.
- If not used immediately, reconstituted BYFAVO may be stored in the vial for up to 8 hours under controlled room temperature at 20°C to 25°C (68°F to 77°F). After 8 hours, any unused portion must be discarded.

2.4 Administration with Other Fluids

- BYFAVO has been shown to be compatible with the following intravenous fluids:
  - 0.9% Sodium Chloride Injection, USP
  - 5% Dextrose Injection, USP
  - 20% Dextrose Injection, USP
  - 5% Dextrose and 0.45% Sodium Chloride Injection, USP.
- BYFAVO has also been shown to be compatible with Ringer's Solution, a solution containing Sodium Chloride, Potassium Chloride and Calcium Chloride Dihydrate.
- BYFAVO has been shown to be incompatible with the following intravenous fluids:
  - Lactated Ringer's Solution, a solution containing Sodium Chloride, Sodium Lactate, Potassium Chloride, and Calcium Chloride Dihydrate. Lactated Ringer's Solution is also known as Ringer's Lactate Solution, Compound Sodium Lactate Solution, and Hartmann's Solution.
  - Acetated Ringer's Solution, a solution containing Sodium Chloride, Sodium Acetate, Potassium Chloride, and Calcium Chloride Dihydrate.
- BYFAVO compatibility with other agents has not been adequately evaluated.
- Do not mix BYFAVO with other drugs or fluids prior to administration.

3 DOSAGE FORM AND STRENGTHS

Single-patient-use vial: Each glass, single-patient-use vial of BYFAVO (remimazolam) for injection contains 20 mg remimazolam white to off-white lyophilized powder, equivalent to 27.2 mg remimazolam besylate.

4 CONTRAINDICATIONS

BYFAVO is contraindicated in patients with a history of severe hypersensitivity reaction to dextran 40 or products containing dextran 40 [see Warnings and Precautions (5.3)].

5 WARNINGS AND PRECAUTIONS

5.1 Personnel and Equipment for Monitoring and Resuscitation

Clinically notable hypoxia, bradycardia, and hypotension were observed in Phase 3 studies of BYFAVO. Continuously monitor vital signs during sedation and through the recovery period.

Only personnel trained in the administration of procedural sedation, and not involved in the conduct of the diagnostic or therapeutic procedure, should administer BYFAVO.

Administering personnel must be trained in the detection and management of airway obstruction, hypoventilation, and apnea, including the maintenance of a patent airway, supportive ventilation, and cardiovascular resuscitation.

Resuscitative drugs, and age- and size-appropriate equipment for bag/valve/mask assisted ventilation must be immediately available during administration of BYFAVO [see Dosage and Administration (2.1)].

Consider the potential for worsened cardiorespiratory depression prior to using BYFAVO concomitantly with other drugs that have the same potential (e.g., opioid analgesics or other sedative-hypnotics) [see Drug Interactions (7.1)].

Administer supplemental oxygen to sedated patients through the recovery period.

A benzodiazepine reversal agent (flumazenil) should be immediately available during administration of BYFAVO [see Overdosage (10)].

5.2 Risks from Concomitant Use with Opioid Analgesics and Other Sedative-Hypnotics

Concomitant use of benzodiazepines, including BYFAVO, and opioid analgesics may result in profound sedation, respiratory depression, coma, and death [see Drug Interactions (7.1)].

The sedative effect of intravenous BYFAVO can be accentuated by concomitantly administered CNS depressant medications, including other benzodiazepines and propofol.

Titrate the dose of BYFAVO when administered with opioid analgesics and sedative-hypnotics to the desired clinical response.

Continuously monitor sedated patients for hypotension, airway obstruction, hypoventilation, apnea, and oxygen desaturation. These cardiorespiratory effects may be more likely to occur in patients with obstructive sleep apnea, the elderly, and ASA III or IV patients.

5.3 Hypersensitivity Reactions

BYFAVO contains dextran 40, which can cause hypersensitivity reactions, including rash, urticaria, pruritus, and anaphylaxis. BYFAVO is contraindicated in patients with a history of severe hypersensitivity reaction to dextran 40 or products containing dextran 40 [see Contraindications (4), Adverse Reactions (6)].

5.4 Neonatal Sedation and Withdrawal Syndrome

Receiving benzodiazepines late in pregnancy can result in sedation (respiratory depression, lethargy, hypotonia) and/or withdrawal symptoms (hyperreflexia, irritability, restlessness, tremors, inconsolable crying, and feeding difficulties) in the neonate. Monitor neonates exposed to benzodiazepines, including BYFAVO, during pregnancy or labor for signs of sedation and monitor neonates exposed to benzodiazepines during pregnancy for signs of withdrawal and manage these neonates accordingly [see Use in Specific Populations (8.1)].

5.5 Pediatric Neurotoxicity

Published animal studies demonstrate that the administration of anesthetic and sedation drugs that block NMDA receptors and/or potentiate GABA activity increase neuronal apoptosis in the developing brain and result in long-term cognitive deficits when used for longer than 3 hours.

The clinical significance of these findings is not clear. However, based on the available data, the window of vulnerability to these changes is believed to correlate with exposures in the third trimester of gestation through the first several months of life, but may extend out to approximately three years of age in humans [see Use in Specific Populations (8.1, 8.4), Nonclinical Pharmacology (13.2)].

Some published studies in children suggest that similar deficits may occur after repeated or prolonged exposures to anesthetic agents early in life and may result in adverse cognitive or behavioral effects. These studies have substantial limitations, and it is not clear if the observed effects are due to the anesthetic/sedation drug administration or other factors such as the surgery or underlying illness.

Anesthetic and sedation drugs are a necessary part of the care of children needing surgery, other procedures, or tests that cannot be delayed, and no specific medications have been shown to be safer than any other. Decisions regarding the timing of any elective procedures requiring anesthesia should take into consideration the benefits of the procedure weighed against the potential risks.

6 ADVERSE REACTIONS

The following serious adverse reactions are discussed in greater detail in other sections:

- Neonatal Sedation and Withdrawal Syndrome [see Warnings and Precautions (5.4), Use in Specific Populations (8.1)]

6.1 Clinical Trials Experience

Because clinical trials are conducted under widely varying conditions, adverse reaction rates observed in the clinical trials of a drug cannot be directly compared to rates in the clinical trials of another drug and may not reflect the rates observed in practice.

The safety of BYFAVO was evaluated in three prospective, randomized, double-blind, multicenter, parallel group clinical studies in 630 patients undergoing colonoscopy (two studies) or bronchoscopy (one study). Colonoscopy Study 1 and the bronchoscopy study evaluated American Society of Anesthesiologists (ASA) physical status I to III patients, and Colonoscopy Study 2 evaluated ASA III and IV patients.

All three studies evaluated the safety of BYFAVO compared to placebo with midazolam rescue and an open-label midazolam treatment arm. Patients were administered a total dose ranging from 5 to 30 mg of BYFAVO. In these studies, the most common adverse reactions (incidence greater than 10%) following BYFAVO administration were hypotension, hypertension, diastolic hypertension, systolic hypertension, hypoxia, and diastolic hypotension. There were two patients who experienced an adverse reaction that led to discontinuation of study drug. One patient in the BYFAVO arm in the bronchoscopy study discontinued treatment due to bradycardia, hypertension, hypotension, hypoxia, and respiratory rate increase. One patient in the open-label midazolam arm in Colonoscopy Study 2 discontinued due to respiratory acidosis. No deaths were reported during the studies.

Tables 1-3 provide a summary of the common adverse reactions observed in each of the three Phase 3 studies with BYFAVO.

Table 1: Common Adverse Reactions in Colonoscopy Study 1 (Incidence >2%), ASA I to III
Adverse Reaction | BYFAVO N = 296 | Placebo (with Midazolam Rescue [57/60 (95%) patients received midazolam rescue.]) N = 60 | Midazolam N = 102
Adverse Reaction | n (%) | n (%) | n (%)
Hypotension [Hypotension defined as a fall in systolic BP to ≤80 mmHg or in diastolic BP to ≤40 mmHg, or a fall in systolic or diastolic BP of 20% or more below baseline or necessitating medical intervention.] | 115 (39%) | 25 (42%) | 63 (62%)
Hypertension [Hypertension defined as an increase in systolic BP to ≥180 mmHg or in diastolic BP to ≥100 mmHg, or an increase of systolic or diastolic BP of 20% or more over baseline or necessitating medical intervention.] | 59 (20%) | 17 (28%) | 18 (18%)
Bradycardia | 33 (11%) | 7 (12%) | 16 (16%)
Diastolic hypertension | 29 (10%) | 6 (10%) | 9 (9%)
Tachycardia | 23 (8%) | 7 (12%) | 13 (13%)
Diastolic hypotension | 23 (8%) | 4 (7%) | 9 (9%)
Systolic hypertension | 16 (5%) | 5 (8%) | 6 (6%)

Table 2: Common Adverse Reactions in Bronchoscopy Study (Incidence >2%)
Adverse Reaction | BYFAVO N = 303 | Placebo (with Midazolam Rescue [57/59 (97%) patients received midazolam rescue.]) N = 59 | Midazolam N = 69
Adverse Reaction | n (%) | n (%) | n (%)
Hypotension [Hypotension defined as a fall in systolic BP to ≤80 mmHg or in diastolic BP to ≤40 mmHg, or a fall in systolic or diastolic BP of 20% or more below baseline or necessitating medical intervention.] | 99 (33%) | 28 (47%) | 23 (33%)
Hypertension [Hypertension defined as an increase in systolic BP to ≥180 mmHg or in diastolic BP to ≥100 mmHg, or an increase of systolic or diastolic BP of 20% or more over baseline or necessitating medical intervention.] | 85 (28%) | 9 (15%) | 19 (28%)
Diastolic hypertension | 77 (25%) | 15 (25%) | 16 (23%)
Systolic hypertension | 67 (22%) | 13 (22%) | 17 (25%)
Hypoxia | 66 (22%) | 12 (20%) | 13 (19%)
Respiratory rate increased | 43 (14%) | 6 (10%) | 10 (14%)
Diastolic hypotension | 41 (14%) | 17 (29%) | 16 (23%)
Nausea | 12 (4%) | 2 (3%) | 2 (3%)
Bradycardia | 11 (4%) | 4 (7%) | 4 (6%)
Pyrexia | 11 (4%) | 1 (2%) | 1 (1%)
Headache | 8 (3%) | 0 (0%) | 3 (4%)

Table 3: Common Adverse Reactions in Colonoscopy Study 2 (Incidence >2%), ASA III and IV
Adverse Reaction | BYFAVO N = 31 | Placebo (with Midazolam Rescue [16/16 (100%) patients received midazolam rescue.]) N = 16 | Midazolam N = 30
Adverse Reaction | n (%) | n (%) | n (%)
Hypotension [Hypotension defined as a fall in systolic BP to ≤80 mmHg or in diastolic BP to ≤40 mmHg, or a fall in systolic or diastolic BP of 20% or more below baseline or necessitating medical intervention.] | 18 (58%) | 11 (69%) | 17 (57%)
Hypertension [Hypertension defined as an increase in systolic BP to ≥180 mmHg or in diastolic BP to ≥100 mmHg, or an increase of systolic or diastolic BP of 20% or more over baseline or necessitating medical intervention.] | 13 (42%) | 6 (38%) | 13 (43%)
Respiratory acidosis | 6 (19%) | 2 (13%) | 8 (27%)
Diastolic hypertension | 3 (10%) | 0 (0%) | 0 (0%)
Systolic hypertension | 2 (6%) | 0 (0%) | 0 (0%)
Bradycardia | 1 (3%) | 1 (6%) | 4 (13%)
Respiratory rate decreased | 1 (3%) | 1 (6%) | 2 (7%)
Diastolic hypotension | 1 (3%) | 1 (6%) | 0 (0%)
Blood pressure diastolic increased | 1 (3%) | 0 (0%) | 0 (0%)
Blood pressure increased | 1 (3%) | 0 (0%) | 0 (0%)
Blood pressure systolic increased | 1 (3%) | 0 (0%) | 0 (0%)
Upper respiratory tract infection | 1 (3%) | 0 (0%) | 0 (0%)

Adverse reaction data from Colonoscopy Study 1 and the bronchoscopy study analyzed according to the cumulative dose of concomitant fentanyl (<100 mcg, 100-150 mcg and >150 mcg) suggest an increase in some adverse reactions with increasing fentanyl dose, such as hypotension, hypertension, bradycardia, hypoxia, and increased respiratory rate (see Table 4 and Table 5). There were too few patients in each fentanyl stratum in Colonoscopy Study 2 to perform this analysis.

Table 4: Common Adverse Reactions [Incidence >2% of patients.] in Colonoscopy Study 1 by Cumulative Fentanyl Dose
 | BYFAVO |  |  | Placebo (with Midazolam Rescue [57/60 (95%) patients received midazolam rescue.]) |  |  | Midazolam
Fentanyl dose (mcg) | <100 | 100-150 | >150 | <100 | 100-150 | >150 | <100 | 100-150 | >150
 | N = 148 | N = 146 | N = 2 | N = 9 | N = 43 | N = 8 | N = 31 | N = 62 | N = 9
Adverse Reaction | n (%) | n (%) | n (%) | n (%) | n (%) | n (%) | n (%) | n (%) | n (%)
Hypotension [Hypotension defined as a fall in systolic BP to ≤80 mmHg or in diastolic BP to ≤40 mmHg, or a fall in systolic or diastolic BP of 20% or more below baseline or necessitating medical intervention.] | 49 (33%) | 64 (44%) | 2 (100%) | 5 (56%) | 17 (40%) | 3 (38%) | 18 (58%) | 36 (58%) | 9 (100%)
Hypertension [Hypertension defined as an increase in systolic BP to ≥180 mmHg or in diastolic BP to ≥100 mmHg, or an increase of systolic or diastolic BP of 20% or more over baseline or necessitating medical intervention.] | 24 (16%) | 35 (24%) | 0 (0%) | 1 (11%) | 14 (33%) | 2 (25%) | 3 (10%) | 12 (19%) | 3 (33%)
Bradycardia | 12 (8%) | 20 (14%) | 1 (50%) | 0 (0%) | 5 (12%) | 2 (25%) | 1 (3%) | 13 (21%) | 2 (22%)
Diastolic hypertension | 9 (6%) | 20 (14%) | 0 (0%) | 0 (0%) | 3 (7%) | 3 (38%) | 2 (6%) | 7 (11%) | 0 (0%)
Tachycardia | 10 (7%) | 12 (8%) | 1 (50%) | 0 (0%) | 6 (14%) | 1 (13%) | 2 (6%) | 8 (13%) | 3 (33%)
Diastolic hypotension | 10 (7%) | 13 (9%) | 0 (0%) | 0 (0%) | 3 (7%) | 1 (13%) | 3 (10%) | 4 (6%) | 2 (22%)
Systolic hypertension | 5 (3%) | 11 (8%) | 0 (0%) | 0 (0%) | 3 (7%) | 2 (25%) | 4 (13%) | 2 (3%) | 0 (0%)

Table 5: Common Adverse Reactions [Incidence >2% of patients.] in Bronchoscopy Study by Cumulative Fentanyl Dose
 | BYFAVO |  |  | Placebo (with Midazolam Rescue [57/59 (97%) patients received midazolam rescue.]) |  |  | Midazolam
Fentanyl dose (mcg) | <100 | 100-150 | >150 | <100 | 100-150 | >150 | <100 | 100-150 | >150
 | N = 215 | N = 63 | N = 25 | N = 26 | N = 18 | N = 15 | N = 29 | N = 27 | N = 13
Adverse Reaction | n (%) | n (%) | n (%) | n (%) | n (%) | n (%) | n (%) | n (%) | n (%)
Hypotension [Hypotension defined as a fall in systolic BP to ≤ 80 mmHg or in diastolic BP to ≤40 mmHg, or a fall in systolic or diastolic BP of 20% or more below baseline or necessitating medical intervention.] | 52 (24%) | 32 (51%) | 16 (64%) | 7 (27%) | 9 (50%) | 12 (80%) | 7 (24%) | 7 (26%) | 9 (69%)
Hypertension [Hypertension defined as an increase in systolic BP to ≥180 mmHg or in diastolic BP to ≥100 mmHg, or an increase of systolic or diastolic BP of 20% or more over baseline or necessitating medical intervention.] | 43 (20%) | 25 (40%) | 18 (72%) | 2 (8%) | 2 (11%) | 5 (33%) | 3 (10%) | 8 (30%) | 8 (62%)
Diastolic hypertension | 65 (30%) | 12 (19%) | 0 (0%) | 11 (42%) | 3 (17%) | 1 (7%) | 10 (34%) | 6 (22%) | 0 (0%)
Systolic hypertension | 55 (26%) | 11 (17%) | 1 (4%) | 10 (38%) | 3 (17%) | 0 (0%) | 9 (31%) | 6 (22%) | 2 (15%)
Hypoxia | 35 (16%) | 22 (35%) | 9 (36%) | 6 (23%) | 2 (11%) | 4 (27%) | 2 (7%) | 5 (19%) | 6 (46%)
Respiratory rate increased | 22 (10%) | 12 (19%) | 9 (36%) | 1 (4%) | 2 (11%) | 3 (20%) | 2 (7%) | 5 (19%) | 3 (23%)
Diastolic hypotension | 28 (13%) | 13 (21%) | 0 (0%) | 8 (31%) | 7 (39%) | 2 (13%) | 7 (24%) | 6 (22%) | 3 (23%)
Nausea | 9 (4%) | 1 (2%) | 2 (8%) | 0 (0%) | 0 (0%) | 2 (13%) | 1 (3%) | 1 (4%) | 0 (0%)
Bradycardia | 3 (1%) | 4 (6%) | 4 (16%) | 2 (8%) | 1 (6%) | 1 (7%) | 0 (0%) | 2 (7%) | 2 (15%)
Pyrexia | 7 (3%) | 2 (3%) | 2 (8%) | 0 (0%) | 0 (0%) | 1 (7%) | 1 (3%) | 0 (0%) | 0 (0%)
Headache | 5 (2%) | 2 (3%) | 1 (4%) | 0 (0%) | 0 (0%) | 0 (0%) | 0 (0%) | 3 (11%) | 0 (0)%

7 DRUG INTERACTIONS

7.1 Opioid Analgesics and Other Sedative-Hypnotics

The sedative effect of intravenous BYFAVO can be accentuated by concomitantly administered CNS depressant medications, including opioid analgesics, other benzodiazepines, and propofol. Continuously monitor vital signs during sedation and through the recovery period. Titrate the dose of BYFAVO when administered with opioid analgesics and sedative-hypnotics to the desired clinical response [see Warnings and Precautions (5.2)].

8 USE IN SPECIFIC POPULATIONS

8.1 Pregnancy

Risk Summary

Neonates born to mothers using benzodiazepines late in pregnancy have been reported to experience symptoms of sedation and/or neonatal withdrawal [see Warnings and Precautions (5.4), Clinical Considerations]. Available data from published observational studies of pregnant women exposed to benzodiazepines do not report a clear association with benzodiazepines and major birth defects (see Data).

In animal studies, reduced fetal weights but no evidence of malformations or embryofetal lethality were noted in a study in which pregnant rabbits were treated intravenously with 4 times the maximum recommended human dose (MRHD) of 30 mg during organogenesis. Adequate rodent reproductive and developmental toxicology studies have not been completed to fully evaluate the effects of BYFAVO.

Published studies in pregnant primates demonstrate that the administration of anesthetic and sedation drugs that block NMDA receptors and/or potentiate GABA activity during the period of peak brain development increases neuronal apoptosis in the developing brain of the offspring when used for longer than 3 hours. There are no data on pregnancy exposures in primates corresponding to periods prior to the third trimester in humans (see Data).

The background risk of major birth defects and miscarriage for the indicated population is unknown. All pregnancies have a background risk of birth defect, loss, or other adverse outcomes. In the U.S. general population, the estimated background risk of major birth defects and miscarriage in clinically recognized pregnancies is 2 to 4% and 15 to 20%, respectively.

Clinical Considerations

Fetal/Neonatal Adverse Reactions

Benzodiazepines cross the placenta and may produce respiratory depression, hypotonia, and sedation in neonates. Monitor neonates exposed to BYFAVO during pregnancy or labor for signs of sedation, respiratory depression, hypotonia, and feeding problems. Monitor neonates exposed to BYFAVO during pregnancy for signs of withdrawal. Manage these neonates accordingly [see Warnings and Precautions (5.4)].

Data

Human Data

Published data from observational studies on the use of benzodiazepines during pregnancy do not report a clear association with benzodiazepines and major birth defects. Although early studies reported an increased risk of congenital malformations with diazepam and chlordiazepoxide, there was no consistent pattern noted. In addition, the majority of more recent case-control and cohort studies of benzodiazepine use during pregnancy, which were adjusted for confounding exposures to alcohol, tobacco, and other medications, have not confirmed these findings.

Animal Data

Reduced fetal weights but no evidence of malformation or embryofetal lethality were noted in a study in which pregnant rabbits were treated intravenously with 5 mg/kg remimazolam (approximately 4 times the MRHD of 30 mg/day based on AUC) from Gestation Day 6 to 20 in the presence of maternal toxicity (reduced food intake and body weights).

In a study that did not test exposures comparable to the MRHD of 30 mg/day over the full period of organogenesis, there was an increase in early resorptions (embryolethality) but no evidence of malformations when female rats were treated from Gestation Day 6 through 17 with up to 30 mg/kg remimazolam via intravenous bolus (approximately 0.3 times the MRHD based on AUC by the end of the dosing interval) in the presence of maternal toxicity (convulsion in one mid dose and one high dose dam).

In a pre- and postnatal development study that did not test exposures comparable to the MRHD of 30 mg/day over the full treatment period, there were no adverse effects on survival or development of offspring when pregnant rats were treated with up to 30 mg/kg remimazolam (<0.3 times the MRHD by the end of the gestational period) by intravenous bolus injection from Gestation Day 6 through Lactation Day 20 with minimal evidence of maternal toxicity (sedation).

No evidence of adverse effects on physical development, a functional observational battery of behavioral assessments, or fertility were noted in pups born to pregnant rabbits that were treated by intravenous infusion of up to 20 mg/kg/day remimazolam (approximately 19 times the MRHD based on AUC) from 14 days prior to mating until Lactation Day 30 despite the presence of maternal toxicity (sedation, convulsions, and mortality). Learning and memory of the first-generation offspring was not evaluated in this study.

In a published study in primates, administration of an anesthetic dose of ketamine for 24 hours on Gestation Day 122 increased neuronal apoptosis in the developing brain of the fetus. In other published studies, administration of either isoflurane or propofol for 5 hours on Gestation Day 120 resulted in increased neuronal and oligodendrocyte apoptosis in the developing brain of the offspring. With respect to brain development, this time period corresponds to the third trimester of gestation in the human. The clinical significance of these findings is not clear; however, studies in juvenile animals suggest neuroapoptosis correlates with long-term cognitive deficits [see Warnings and Precautions (5.4, 5.5), Use in Specific Populations (8.4), Nonclinical Toxicology (13.2)].

8.2 Lactation

Risk Summary

There are reports of sedation, poor feeding, and poor weight gain in infants exposed to benzodiazepines through breast milk. There are no data on the effects of remimazolam in human milk, the effects on the breastfed infant or the effects on milk production. Remimazolam is present in animal milk (see Data). When a drug is present in animal milk, it is likely that it will be present in human milk.

The developmental and health benefits of breastfeeding should be considered along with the mother’s clinical need for BYFAVO and any potential adverse effects on the breastfed child from BYFAVO or from the underlying maternal condition.

Clinical Considerations

Infants exposed to BYFAVO through breast milk should be monitored for sedation, poor feeding, and poor weight gain. A lactating woman may consider interrupting breastfeeding and pumping and discarding breast milk during treatment and for 5 hours (approximately 5 elimination half-lives) after BYFAVO administration in order to minimize drug exposure to a breastfed infant.

Data

In rabbits administered daily intravenous infusions of remimazolam at 12.5 and 20 mg/kg/day from 14 days before mating until Lactation Day 30, remimazolam and the metabolite CNS7054 were present in milk samples obtained after the end of an infusion on Day 10 or 11 of lactation. Remimazolam was not quantifiable in plasma samples obtained from rabbit kits taken in the morning on Day 10 or 11 of lactation. However, metabolite CNS7054 was present at low levels in 2 of the 5 kits sampled.

8.4 Pediatric Use

Safety and effectiveness in pediatric patients have not been established. No studies are available in any pediatric population and extrapolation of adult effectiveness data to the pediatric population is not possible.

Published juvenile animal studies demonstrate that the administration of anesthetic and sedation drugs, such as BYFAVO, that either block NMDA receptors or potentiate the activity of GABA during the period of rapid brain growth or synaptogenesis, results in widespread neuronal and oligodendrocyte cell loss in the developing brain and alterations in synaptic morphology and neurogenesis. Based on comparisons across species, the window of vulnerability to these changes is believed to correlate with exposures in the third trimester of gestation through the first several months of life but may extend out to approximately 3 years of age in humans.

In primates, exposure to 3 hours of ketamine that produced a light surgical plane of anesthesia did not increase neuronal cell loss; however, treatment regimens of 5 hours or longer of isoflurane increased neuronal cell loss. Data from isoflurane-treated rodents and ketamine-treated primates suggest that the neuronal and oligodendrocyte cell losses are associated with prolonged cognitive deficits in learning and memory. The clinical significance of these nonclinical findings is not known, and healthcare providers should balance the benefits of appropriate anesthesia in pregnant women, neonates, and young children who require procedures with the potential risks suggested by the nonclinical data [see Warnings and Precautions (5.4), Warnings and Precautions (5.5), Use in Specific Populations (8.1), Nonclinical Toxicology (13.2)].

8.5 Geriatric Use

Of the total number of subjects treated with BYFAVO in clinical studies for procedural sedation, there were 649 subjects <65 years of age, 221 subjects >65 years of age, 171 subjects between 65-74 years of age, and 50 subjects >75 years of age.

No overall differences in safety or effectiveness were observed between these subjects and younger subjects, and other reported clinical experience has not identified differences in responses between the elderly and younger patients. Some data suggest a potential of greater sensitivity (a faster onset of loss of consciousness and a longer duration of sedation) of some older individuals.

Administer supplemental doses of BYFAVO slowly to achieve the level of sedation required for the procedure, and monitor all patients for cardiorespiratory complications.

8.6 Hepatic Impairment

In patients with severe hepatic impairment, the dose of BYFAVO should be carefully titrated to effect. Depending on the overall status of the patient, lower frequency of supplemental doses may be needed to achieve the level of sedation required for the procedure. All patients should be monitored for sedation-related cardiorespiratory complications [see Clinical Pharmacology (12.3)].

9 DRUG ABUSE AND DEPENDENCE

9.1 Controlled Substance

BYFAVO contains remimazolam, a Schedule IV controlled substance (CIV).

9.2 Abuse

BYFAVO contains the benzodiazepine, remimazolam. Benzodiazepines are a class of sedative drugs with a known potential for abuse. Abuse is the intentional, non-therapeutic use of a drug, even once, for its desirable psychological or physiological effects. In a human abuse potential study conducted in recreational sedative abusers (n = 39), remimazolam (5 and 10 mg, IV) produced responses on positive subjective measures such as "Drug Liking," "Overall Drug Liking," "Take Drug Again," and "Good Drug Effects" that were statistically similar to those produced by the sedative midazolam (2.5 and 5 mg), and statistically greater than the responses on these measures that were produced by placebo.

9.3 Dependence

Physical dependence is a state that develops as a result of physiological adaptation in response to repeated drug use, manifested by withdrawal signs and symptoms after abrupt discontinuation or a significant dose reduction of a drug. In a monkey physical dependence study, chronic administration of remimazolam produced withdrawal signs such as tremors, muscle rigidity, restlessness, impaired motor activity, and a reduction in food consumption upon drug discontinuation. One monkey of six in this study exhibited systemic convulsions and dissociation from the environment. These behaviors are consistent with benzodiazepine withdrawal, which suggests that remimazolam produces physical dependence.

10 OVERDOSAGE

Clinical Presentation

Overdosage of benzodiazepines is characterized by central nervous system depression ranging from drowsiness to coma. In mild to moderate cases, symptoms can include drowsiness, confusion, dysarthria, lethargy, hypnotic state, diminished reflexes, ataxia, and hypotonia. Rarely, paradoxical or disinhibitory reactions (including agitation, irritability, impulsivity, violent behavior, confusion, restlessness, excitement, and talkativeness) may occur. In severe overdosage cases, patients may develop respiratory depression and coma. Overdosage of benzodiazepines in combination with other CNS depressants (including alcohol and opioids) may be fatal [see Warnings and Precautions (5.2)]. Markedly abnormal (lowered or elevated) blood pressure, heart rate, or respiratory rate raise the concern that additional drugs and/or alcohol are involved in the overdosage.

Management of Overdosage

In managing benzodiazepine overdosage, employ general supportive measures, including intravenous fluids and airway management. Flumazenil, a specific benzodiazepine receptor antagonist indicated for the complete or partial reversal of the sedative effects of benzodiazepines in the management of benzodiazepine overdosage, can lead to withdrawal and adverse reactions, including seizures, particularly in the context of mixed overdosage with drugs that increase seizure risk (e.g., tricyclic and tetracyclic antidepressants) and in patients with long-term benzodiazepine use and physical dependency. The risk of withdrawal seizures with flumazenil use may be increased in patients with epilepsy. Flumazenil is contraindicated in patients who have received a benzodiazepine for control of a potentially life-threatening condition (e.g., status epilepticus). If the decision is made to use flumazenil, it should be used as an adjunct to, not as a substitute for, supportive management of benzodiazepine overdosage. See the flumazenil injection Prescribing Information.

Consider contacting the Poison Help Line (1-800-222-1222), or medical toxicologist for additional overdosage management recommendations.

11 DESCRIPTION

Each glass, single-patient-use, sterile vial of BYFAVO (remimazolam) for injection contains 20 mg remimazolam, equivalent to 27.2 mg remimazolam besylate.

Remimazolam is a benzodiazepine. Its chemical description is 4H-imidazol[1,2-a][1,4]benzodiazepine-4-propionic acid, 8-bromo-1-methyl-6-(2-pyridinyl)-(4S)-, methyl ester, benzenesulfonate (1:1). The structural formulas are shown below.

Molecular weight of BYFAVO (free base): 439.3 g/mol.

Molecular weight of BYFAVO besylate: 597.5 g/mol.

BYFAVO besylate powder is sparingly soluble in water.

BYFAVO 20 mg contains: 82 mg dextran 40 and 55 mg lactose monohydrate as bulking agents/stabilizers. The pH is adjusted with hydrochloride/sodium hydroxide. Upon reconstitution with saline, BYFAVO has a pH of 2.9 to 3.9.

12 CLINICAL PHARMACOLOGY

12.1 Mechanism of Action

BYFAVO is a benzodiazepine. BYFAVO binds to brain benzodiazepine sites (gamma amino butyric acid type A [GABAA] receptors), while its carboxylic acid metabolite (CNS7054) has a 300 times lower affinity for the receptor. BYFAVO, like other benzodiazepines, did not show clear selectivity between subtypes of the GABAA receptor.

12.2 Pharmacodynamics

Dose finding studies determined the IV dosing recommendation of the initial 5 mg bolus, followed by 2.5 mg top-up doses. Median time to peak sedation, defined as the lowest Modified Observer's Assessment of Alertness/Sedation (MOAA/S) score after the initial dose, in the Phase 3 trials was 3 to 3.5 minutes and median time to fully alert, defined as time to the first of three consecutive MOAA/S scores of five, following the last dose of BYFAVO was 11 to 14 minutes.

Cardiac Electrophysiology

In a thorough QT study, 57 healthy volunteers were given an IV push of 10 mg or 20 mg BYFAVO, intravenous midazolam (2.5 mg or 7.5 mg) or placebo, or a single tablet of moxifloxacin 400 mg given orally. The largest mean placebo-adjusted change-from-baseline QTc (upper bound of 2-sided 90% confidence interval) was 6.7 (9.5) ms, 10.7 (13.4) ms, 4.5 (7.3) ms, and 8.1 (10.8) ms, respectively, after treatment with 10 mg or 20 mg BYFAVO, or 2.5 mg or 7.5 mg midazolam.

BYFAVO treatment is associated with increases in heart rate. The largest mean placebo-adjusted change-from-baseline HR (upper bound of 2-sided 90% confidence interval) was 12.3 (14.2) bpm and 15.2 (17.1) bpm, respectively, after treatment with 10 mg and 20 mg BYFAVO.

12.3 Pharmacokinetics

- BYFAVO has a terminal elimination half-life from plasma of 37 to 53 minutes.
- Mean distribution half-life (t1/2α) is between 0.5 and 2 minutes.
- Half-life (t1/2) is prolonged with increasing severity of hepatic impairment leading to a need for careful dose titration in patients with severe hepatic impairment.
- Clearance (54 to 75 L/h) is not related to body weight.
- In healthy subjects at least 80% and in colonoscopy patients 50% to 60% of dose is excreted in urine as inactive metabolite.

Absorption

BYFAVO is administered intravenously. BYFAVO overall maximum plasma concentration (Cmax) after IV administration of 0.01 to 0.5 mg/kg was 189 to 6,960 ng/mL, and overall area under the concentration versus time curve from time 0 to infinity (AUC0-∞) was 12.1 to 452 ng∙h/mL; BYFAVO cumulative dose versus BYFAVO total exposure (AUC0-∞) suggested a close to dose-proportional relationship. Metabolite Cmax was achieved approximately 20-30 minutes post dose. Metabolite AUC0-∞ was 231 to 7,090 ng∙h/mL.

Distribution

BYFAVO volume of distribution (Vz) was 0.76 to 0.98 L/kg. Plasma protein binding of BYFAVO was >91%, primarily to human serum albumin.

Elimination

BYFAVO has a terminal elimination half-life from plasma of 37 to 53 minutes and mean distribution half-life (t1/2α) is between 0.5 and 2 minutes.

Metabolism

The main route of metabolism of BYFAVO is via conversion to primary inactive metabolite CNS7054, which is then subject to hydroxylation and glucuronidation. Conversion to CNS7054 is mediated by tissue carboxylesterases (primarily type 1A), with no meaningful contribution by cytochrome P450 enzymes. The t1/2 of the metabolite was 2.4 to 3.8 hours.

Excretion

In colonoscopy patients, approximately 0.003% BYFAVO is excreted unchanged in urine, and 50% to 60% is excreted in urine as the metabolite CNS7054.

Specific Populations

Pediatric Patients

There were no pediatric patients who received BYFAVO.

Patients with Renal Impairment

The pharmacokinetics of BYFAVO were not altered in patients with mild to end stage renal disease not requiring dialysis. In a renal impairment study, BYFAVO PK parameters (e.g., AUC and Cmax) were not statistically different in subjects with varying degrees of renal function (from normal to severely impaired). Increased exposure to inactive metabolite CNS7054 was observed with increasing degree of renal impairment.

Patients with Hepatic Impairment

A Phase 1 open-label, single-dose trial evaluated the PK and safety of BYFAVO given as an IV bolus of 0.1 mg/kg over 1 minute in subjects with hepatic impairment (8 moderately hepatically impaired subjects and 3 severely hepatically impaired subjects) and 9 matched healthy subjects.

The Cmax values of total BYFAVO were 10% to 20% lower in subjects with hepatic impairment than in healthy subjects. Larger Vz (33% increase in moderately impaired and 41% increase in severely impaired) and Vss (50% increase in moderately impaired and 115% increase in severely impaired), and prolonged t1/2 (60 minutes in moderately impaired and 105 minutes in severely impaired as compared to 42 minutes in healthy subjects), of BYFAVO were observed with increasing severity of hepatic impairment. Sedation lasted longer and recovery took longer for subjects with hepatic impairment compared to healthy subjects. The average duration of loss of consciousness and recovery time was 3.2 minutes and 12.1 minutes, respectively for subjects in the moderately hepatically impaired group. These times were 2.0 minutes and 16.7 minutes, respectively, for the subjects in the severely hepatically impaired group. Healthy control subjects had a loss of consciousness of 1.6 minutes and a recovery time of 8.0 minutes.

In patients with severe hepatic impairment, the dose of BYFAVO should be carefully titrated to effect. Depending on the overall status of the patient, less frequency of supplemental doses may be needed to achieve the level of sedation required for the procedure. All patients should be monitored for sedation-related cardiorespiratory complications.

Other Specific Populations

Age, sex, race, and weight had no clinically relevant effect on BYFAVO pharmacokinetics.

Drug Interactions

BYFAVO and the metabolite CNS7054 caused no relevant inhibition of cytochrome P450 isoenzymes 1A2, 2B6, 2C8, 2C9, 2C19, 2D6, or 3A4. There were no inducing effects on CYP1A2, 2B6, and 3A4. BYFAVO was not a relevant substrate of a panel of human drug transporters (OATP1B1, OATP1B3, BCRP).

No relevant inhibition of human drug transporters (OAT3, OCT2, OATP1B1, OATP1B3, OAT1, BCRP) was seen with BYFAVO or CNS7054. Remifentanil did not influence the hydrolysis of BYFAVO by human liver S9 fractions, reducing the possibility of an interaction by competition for liver carboxylesterases.

These results together show a very low potential of BYFAVO for pharmacokinetic drug interactions.

13 NONCLINICAL TOXICOLOGY

13.1 Carcinogenesis, Mutagenesis, Impairment of Fertility

Carcinogenesis

Long-term animal studies have not been performed to evaluate the carcinogenic potential of remimazolam.

Mutagenesis

Remimazolam was not mutagenic or clastogenic when evaluated in an in vitro bacterial reverse mutation assay (Ames test), an in vivo rat micronucleus assay, mouse lymphoma cells, in vivo rat bone marrow micronucleus assay, or comet assay.

Impairment of Fertility

In a study that did not test exposures comparable to the MRHD of 30 mg/day, there were no adverse effects on male or female fertility when male rats were treated for 28 days prior to mating and female rats were treated for 14 days prior to mating with up to 30 mg/kg remimazolam via intravenous bolus (approximately 0.03 times the MRHD based on AUC).

There was no impact on female fertility when female rabbits were administered remimazolam by intravenous infusion (up to 4 hours/day) up to 20 mg/kg/day (approximately 17 times the MRHD of 30 mg/day based on AUC) from 14 days prior to mating.

No adverse effects on histology of the testes and epididymides or evaluation of spermatid count, sperm motility, and sperm morphology were reported in a repeat-dose toxicity study in which male minipigs were administered remimazolam by intravenous infusion (6 hours) up to 120 mg/kg/day (approximately 400 times the MRHD based on AUC) for 28 days followed by a 14-day recovery period.

13.2 Animal Toxicology and/or Pharmacology

Published studies in animals demonstrate that the use of anesthetic agents during the period of rapid brain growth or synaptogenesis results in widespread neuronal and oligodendrocyte cell loss in the developing brain and alterations in synaptic morphology and neurogenesis. Based on comparisons across species, the window of vulnerability to these changes is believed to correlate with exposures in the third trimester through the first several months of life but may extend out to approximately 3 years of age in humans.

In primates, exposure to 3 hours of an anesthetic regimen that produced a light surgical plane of anesthesia did not increase neuronal cell loss; however, treatment regimens of 5 hours or longer increased neuronal cell loss. Data in rodents and in primates suggest that the neuronal and oligodendrocyte cell losses are associated with subtle but prolonged cognitive deficits in learning and memory. The clinical significance of these nonclinical findings is not known, and healthcare providers should balance the benefits of appropriate anesthesia in neonates and young children who require procedures against the potential risks suggested by the nonclinical data [See Warnings and Precautions (5.4), Use in Specific Populations (8.1, 8.4)].

14 CLINICAL STUDIES

The safety and efficacy of BYFAVO compared to a saline placebo with midazolam rescue treatment group and an open-label midazolam treatment group was evaluated in three randomized, double-blind, multicenter Phase 3 studies conducted in 969 adult patients receiving procedural sedation.

14.1 Colonoscopy Study 1 (NCT 02290873)

This Phase 3 study was conducted in 461 ASA I to III patients undergoing colonoscopy. BYFAVO 5 mg (2 mL) IV was administered as an initial bolus, followed by 2.5 mg (1 mL) top-up doses versus placebo 2 mL administered as an initial bolus, followed by 1 mL top-up doses. Midazolam rescue was dosed per investigator discretion in both treatment groups. Fentanyl was administered as an analgesic pre-treatment at an initial dose of 50 to 75 mcg IV (or a reduced dose for ASA III patients) immediately prior to administration of the initial dose of study medication. Top-up doses of fentanyl 25 mcg every 5 to 10 minutes were allowed until analgesia was adequate or a maximum dose of 200 mcg had been administered. Supplemental oxygen was administered prior to the start of the procedure and continued at a rate of 1 to 5 L/minute until the patient was fully alert after procedure completion. Colonoscopy started when adequate sedation was achieved, defined as an MOAA/S score ≤3. The primary efficacy endpoint for BYFAVO versus placebo was success of the colonoscopy procedure, defined as a composite of the following:

- Completion of the colonoscopy procedure, AND
- No requirement for a rescue sedative medication, AND
- No requirement for more than 5 doses of study medication within any 15-minute window.

There were 63 patients (13.8%) who were aged 65 years or older, 218 patients (47.6%) who were male, 339 (74.0%) who were white, 80 (17.5%) who were Black or African American, 31 (6.8%) who were Asian, and 73 (15.9%) who were Hispanic or Latino. There were 143 patients in ASA I, 285 in ASA II, and 30 in ASA III. As shown in Table 6, the colonoscopy sedation success rate was statistically significantly higher in the BYFAVO group than in the placebo group.

Table 6. Colonoscopy Sedation Success Rate – Colonoscopy Study 1
Cohort | Sedation Success Rate n/N (%)
Remimazolam | 272/298 (91.3%)
Placebo | 1/60 (1.7%)
n/N = number of successes/number of subjects in group.

The reasons for procedural sedation failure are shown in Table 7.

Table 7. Reasons for Procedural Sedation Failure – Colonoscopy Study 1
Reason | Remimazolam N = 298 n (%) | Placebo N = 60 n (%)
Rescue sedative medication taken | 10 (3.4%) | 57 (95%)
Too many doses within the predefined time window | 18 (6.0%) | 44 (73.3%)
Procedure not completed | 7 (2.3%) | 1 (1.7%)

Table 8 shows the number of top-up doses required, and the total doses of study medication, fentanyl, and rescue medication administered.

Table 8. Number of Top-up Doses and Total Doses of Study Medication, Fentanyl, and Rescue Medication – Colonoscopy Study 1
 | Number of Top-up Doses of Study Drug (Mean ± SD) | Total Amount of Study Drug (mg) (Mean ± SD) | Total Amount of Fentanyl (mcg) (Mean ± SD) | Total Amount of Midazolam Rescue Medication (mg) (Mean ± SD)
Remimazolam | 2.2 ± 1.6 | 10.5 ± 4.0 | 88.9 ± 21.7 | 0.3 ± 2.1
Placebo | 5.1 ± 0.5 | 0 | 121.3 ± 34.4 | 6.8 ± 4.2

Summaries of the time to start procedure, duration of procedure, time to fully alert, and time to ready for discharge are shown in Table 9.

Table 9. Time to Start Procedure, Duration of Procedure, Time to Fully Alert, and Time to Ready for Discharge for the Remimazolam Cohort – Colonoscopy Study 1
Time to start procedure (minutes) [Patients who were unable to start the procedure were excluded.]
Median (95% confidence interval) | 4.0 (4.0, 4.0)
Min, Max | 0, 26
Duration of procedure (minutes) [Patients who did not successfully complete the procedure were excluded.]
Median (95% confidence interval) | 12.0 (11.0, 13.0)
Min, Max | 3, 33
Number (proportion) of procedures lasting longer than 30 minutes | 1/291 (0.3%)
Time to fully alert after end of colonoscopy (minutes)
Median (95% confidence interval) | 6.0 (5.0, 7.0)
Min, Max | 0, 44
Time to ready to discharge after end of colonoscopy (minutes)
Median (95% confidence interval) | 44.0 (42.0, 46.0)
Min, Max | 3, 79

14.2 Bronchoscopy Study (NCT 02296892)

This Phase 3 study was conducted in 431 ASA I to III patients undergoing bronchoscopy. BYFAVO 5 mg (2 mL) IV was administered as an initial bolus, followed by 2.5 mg (1 mL) top-up doses versus placebo 2 mL administered as an initial bolus, followed by 1 mL top-up doses. Midazolam rescue was dosed per investigator discretion in both treatment groups. Fentanyl was administered as an analgesic pre-treatment at an initial dose of 25 to 50 mcg IV immediately prior to administration of the initial dose of study medication. Top-up doses of fentanyl 25 mcg every 5 to 10 minutes were allowed until analgesia was adequate. A maximum dose of fentanyl 200 mcg was recommended. Supplemental oxygen was administered prior to the start of the procedure and continued at a rate of 1 to 15 L/minute until the patient was fully alert after procedure completion. Bronchoscopy started when adequate sedation was achieved, defined as an MOAA/S score ≤3. The primary efficacy endpoint for BYFAVO versus placebo was successful sedation for the bronchoscopy procedure, defined as a composite of the following:

- Completion of the bronchoscopy procedure, AND
- No requirement for a rescue sedative medication, AND
- No requirement for more than 5 doses of study medication within any 15-minute window.

There were 209 patients (48.5%) who were 65 years or older, 198 patients (45.9%) who were male, 358 (83.1%) who were white, 62 (14.4%) who were Black or African American, 5 (1.2%) who were Asian, and 8 (1.9%) who were Hispanic or Latino. There were 15 patients in ASA I, 254 in ASA II, and 162 in ASA III. As shown in Table 10, the bronchoscopy sedation success rate was statistically significantly higher for the BYFAVO group than for the placebo group.

Table 10. Bronchoscopy Success Rates
Cohort | Total Success Rate n/N (%)
Remimazolam | 250/310 (80.6%)
Placebo | 3/63 (4.8%)
n/N = number of successes/number of subjects in group.

The reasons for procedural sedation failure are shown in Table 11.

Table 11. Reasons for Procedural Sedation Failure – Bronchoscopy Study
Reason | Remimazolam N = 310 n (%) | Placebo N = 63 n (%)
Rescue sedative medication taken | 49 (15.8%) | 57 (90.5%)
Too many doses within the predefined time window | 14 (4.5%) | 10 (15.9%)
Procedure not completed | 9 (2.9%) | 3 (4.8%)

Table 12 shows the number of top-up doses required, and the total doses of study medication, fentanyl, and rescue medication administered.

Table 12. Number of Top-up Doses and Total Doses of Study Medication, Fentanyl, and Rescue Medication – Bronchoscopy Study
 | Number of Top-up Doses of Study Drug (Mean ± SD) | Total Amount of Study Drug (mg) (Mean ± SD) | Total Amount of Fentanyl (mcg) (Mean ± SD) | Total Amount of Midazolam Rescue Medication (mg) (Mean ± SD)
Remimazolam | 2.6 ± 2.0 | 11.5 ± 5.1 | 81.8 ± 54.3 | 1.3 ± 3.5
Placebo | 4.1 ± 0.8 | 0 | 118.8 ± 79.1 | 5.9 ± 3.7

Summaries of the time to start procedure, duration of procedure, time to fully alert, and time to ready for discharge are shown in Table 13.

Table 13. Time to Start Procedure, Duration of Procedure, Time to Fully Alert and Time to Ready for Discharge for the Remimazolam Cohort – Bronchoscopy Study
Time to start procedure (minutes) [Patients who were unable to start the procedure were excluded.]
Median (95% confidence interval) | 4.1 (4.0, 4.8)
Min, Max | 1,41
Duration of procedure (minutes) [Patients who did not successfully complete the procedure were excluded.]
Median (95% confidence interval) | 10.0 (8.0, 11.0)
Min, Max | 1, 68
Number (proportion) of procedures lasting longer than 30 minutes | 28/299 (9.4%)
Time to fully alert after end of bronchoscopy (minutes)
Median (95% confidence interval) | 6.0 (5.2, 7.1)
Min, Max | 1.1, 107
Time to ready to discharge after end of bronchoscopy (minutes)
Median (95% confidence interval) | 60.0 (57.0, 63.0)
Min, Max | 6.6, 284

14.3 Colonoscopy Study 2 (NCT 02532647)

This Phase 3 study was conducted in 77 ASA III and IV patients undergoing colonoscopy. BYFAVO 2.5 mg (1 mL) to 5 mg (2 mL) IV was administered as an initial bolus, followed by 1.25 mg (0.5 mL) to 2.5 mg (1 mL) top-up doses versus placebo 1 to 2 mL administered with midazolam rescue, dosed per investigator discretion. Fentanyl was administered as an analgesic pre-treatment at an initial maximum dose of 50 mcg (with dose reduction for debilitated patients), immediately prior to administration of the initial dose of study medication. Top-up doses of fentanyl 25 mcg every 5 to 10 minutes were allowed until analgesia was adequate or a maximum dose of 200 mcg had been administered. Supplemental oxygen was administered prior to the start of the procedure and continued at a rate of up to 4 L/minute until the patient was fully alert after procedure completion. Colonoscopy started when adequate sedation was achieved, defined as an MOAA/S score ≤3.

The primary objective of the study was to assess the safety of multiple doses of BYFAVO compared to placebo and midazolam. Procedure success was a secondary objective and was defined as follows:

- Completion of the colonoscopy procedure, AND
- No requirement for a rescue sedative medication, AND
- No requirement for more than 5 doses of study medication within any 15-minute window.

The total patient population, including all randomized patients who received any amount of study medication, comprised 31 patients in the remimazolam group, 16 patients in the placebo group, and 30 patients in the midazolam group. There were two patients, one each in the remimazolam and midazolam treatment groups, who were randomized, but did not receive a dose of study medication.

There were 31 patients (40.2%) who were aged 65 years or older, 43 patients (55.8%) who were male, 57 (74.0%) who were white, 19 (24.7%) who were Black or African American, 1 (1.30%) who was Asian, and none who were Hispanic or Latino. There were 40 patients in ASA III and 37 patients in ASA IV.

Patients in the remimazolam group received a mean (± SD) of 9.0 (± 3.7) mg of remimazolam and a mean (± SD) of 2.5 (± 10.2) mg of midazolam compared to 7.2 (± 2.5) mg in the placebo group. The mean total dose of fentanyl was lower in the remimazolam group (mean ± SD: 59.7 ± 15.4 mcg) than in the placebo group (mean ± SD: 67.2 ± 21.8 mcg).

In the remimazolam group, 90.3% of patients did not receive any rescue sedative medication, compared to 0.0% in the placebo group.

There were no serious adverse reactions and no discontinuations due to adverse reactions observed in the remimazolam group. The incidence of hypotension (SMQ) was 61.3% in the remimazolam group and 75% in the placebo group.

No inferential statistical tests were performed in this trial. Patients who received BYFAVO for sedation during scheduled colonoscopy responded at a numerically greater rate than patients who received placebo (randomized analysis population – remimazolam: 27/32 [84.4%]; placebo: 0/16 [0%]).

16 HOW SUPPLIED/STORAGE AND HANDLING

BYFAVO (remimazolam) for injection, for intravenous use is supplied as follows:

NDC 71390-011-11: Carton of 10 × 12 mL vials. Each 12 mL glass vial of BYFAVO (NDC 71390-011-00) provides a sterile lyophilized white to off-white powder intended for single-patient use only and contains 20 mg remimazolam (equivalent to 27.2 mg remimazolam besylate) ready for reconstitution.

STORAGE AND HANDLING

Store at controlled room temperature 20°C to 25°C (68°F to 77°F) excursions between 15° and 30°C (59° and 86°F) are allowed.

Reconstituted BYFAVO can be stored in the vial for up to 8 hours under controlled room temperature at 20°C to 25°C (68°F to 77°F).

Protect vials from light once they are removed from packaging.

Discard unused portion.

17 PATIENT COUNSELING INFORMATION

Alcohol and Current Medications

Advise patients to notify their healthcare provider about alcohol or medication use. Alcohol and other CNS depressants, such as opioid analgesics and benzodiazepines, can have an additive effect when administered with BYFAVO [see Warnings and Precautions (5.1), Drug Interactions (7.1)].

Pregnancy

Advise pregnant females that receiving BYFAVO late in pregnancy can result in sedation (respiratory depression, lethargy, hypotonia) and/or withdrawal symptoms (hyperreflexia, irritability, restlessness, tremors, inconsolable crying, and feeding difficulties) in newborns. Instruct patients to inform their healthcare provider if they are pregnant during treatment with BYFAVO [see Warnings and Precautions (5.4, 5.5), Use in Specific Populations (8.1)].

Effect of Anesthetic and Sedation Drugs on Early Brain Development

Studies conducted in young animals and children suggest repeated or prolonged use of general anesthetic or sedation drugs in children younger than 3 years may have negative effects on their developing brains. Discuss with parents and caregivers the benefits, risks, and timing and duration of surgery or procedures requiring anesthetic and sedation drugs [see Warnings and Precautions (5.4), Use in Specific Populations (8.1, 8.4), Nonclinical Toxicology (13.2)].

Lactation

Instruct patients to notify their healthcare provider if they are breastfeeding or intend to breastfeed. Instruct breastfeeding patients receiving BYFAVO to monitor infants for excessive sedation, poor feeding and poor weight gain, and to seek medical attention if they notice these signs. A lactating woman may consider pumping and discarding breast milk for 5 hours after receiving BYFAVO during procedural sedation to minimize drug exposure to the breastfed infant [see Use in Specific Populations (8.2)].

Distributed by Acacia Pharma, Inc.
8440 Allison Pointe Blvd., Suite 100
Indianapolis, IN 46250 USA
© 2023 Acacia Pharma, Inc. All rights reserved.

BYF-0006-USPI-01/2023

PRINCIPAL DISPLAY PANEL - 20 mg Vial Carton

NDC 71390-011-11

Rx only

10x20 mg vials

byfavo™
(remimazolam)
for injection
for intravenous use

Recommended dosage:
See prescribing information

20 mg/vial
equivalent to 27.2 mg
remimazolam besylate

CIV

⏵ See package insert for
complete prescribing
information

Preservative free